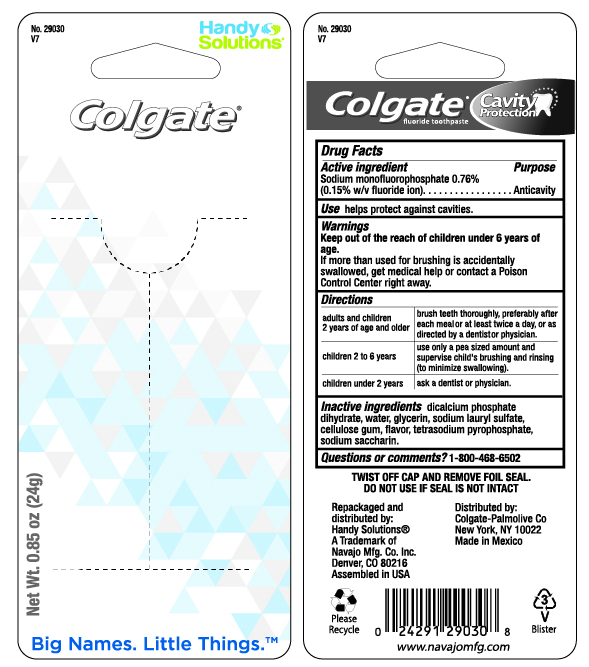 DRUG LABEL: Colgate Great Regular Flavor
NDC: 67751-118 | Form: PASTE, DENTIFRICE
Manufacturer: Navajo Manufacturing Company Inc.
Category: otc | Type: HUMAN OTC DRUG LABEL
Date: 20241003

ACTIVE INGREDIENTS: SODIUM MONOFLUOROPHOSPHATE 1 mg/1 g
INACTIVE INGREDIENTS: SODIUM LAURYL SULFATE 49.14 mg/1 g; WATER; GLYCERIN; DIBASIC CALCIUM PHOSPHATE DIHYDRATE; CARBOXYMETHYLCELLULOSE SODIUM, UNSPECIFIED FORM; SODIUM PYROPHOSPHATE; SACCHARIN SODIUM

Colgate Great Regular Flavor Fluoride Toothpaste

Drug Facts

Active ingredient

Sodium monofluorophosphate 0.76% (0.15% w/v fluoride ion)

Purpose

Anticavity

Use

helps protect against cavities

Warnings

KEEP OUT OF REACH OF CHILDREN

Keep out of the reach of children under 6 years of age.

If more than used for brushing is accidentally swallowed, get medical help or contact a Poison Control Center right away.

Directions

adults and children 2 years of age and older | brush teeth thoroughly, preferably after each meal or at least twice a day, or as directed by a dentist or physician
children 2 to 6 years | use only a pea sized amount and supervise child's brushing and rinsing (to minimize swallowing)
children under 2 years | ask a dentist or physician

Inactive ingredients

dicalcium phosphate dihydrate, water, glycerin, sodium lauryl sulfate, cellulose gum, flavor, tetrasodium pyrophosphate, sodium saccharin

Questions or comments?

Call toll-free 1-800-468-6502